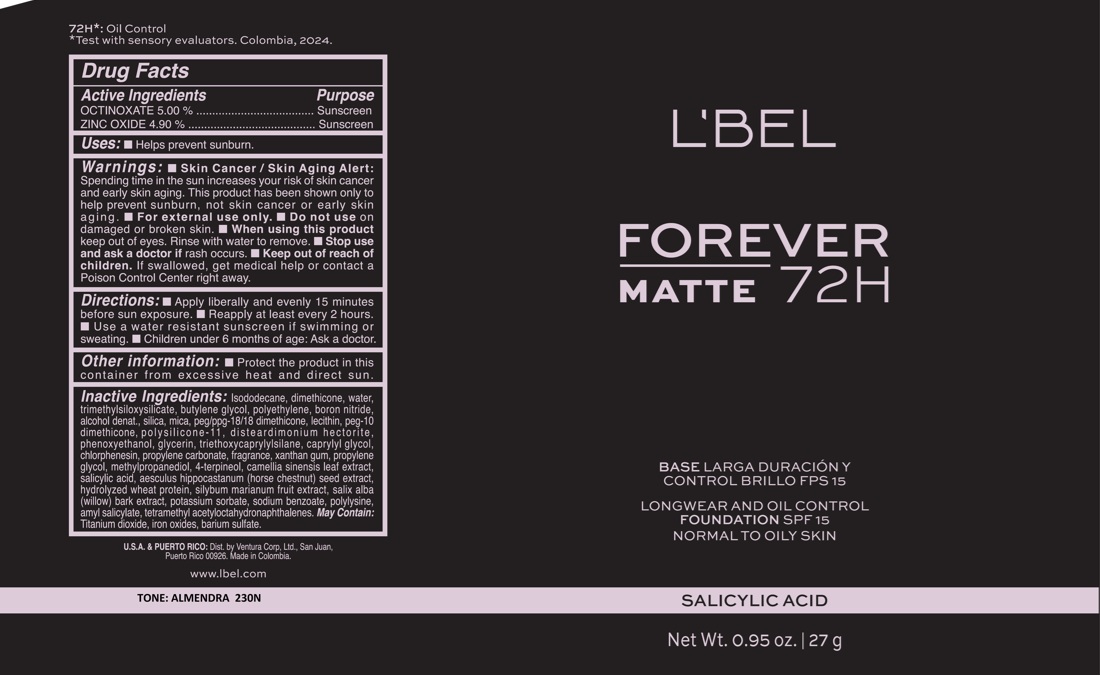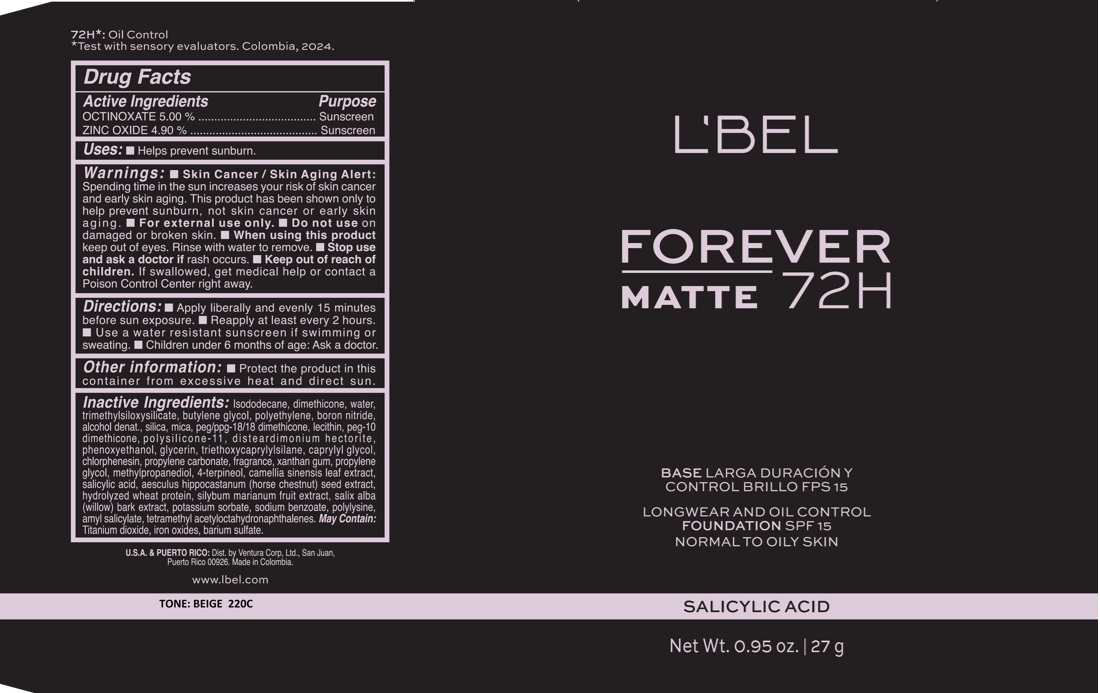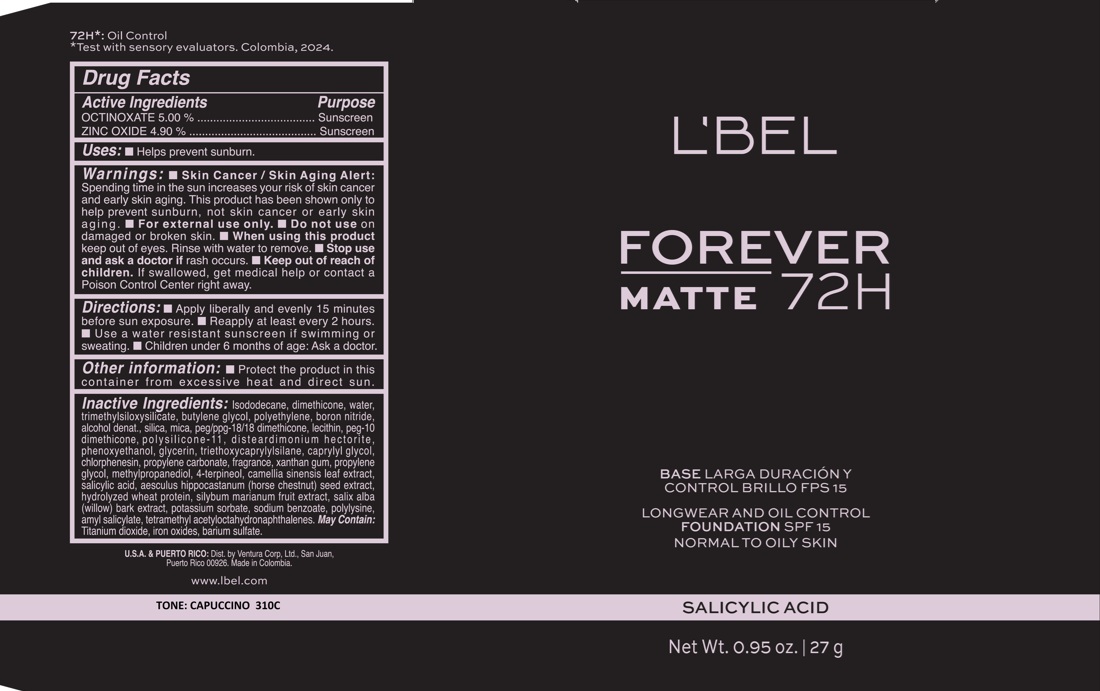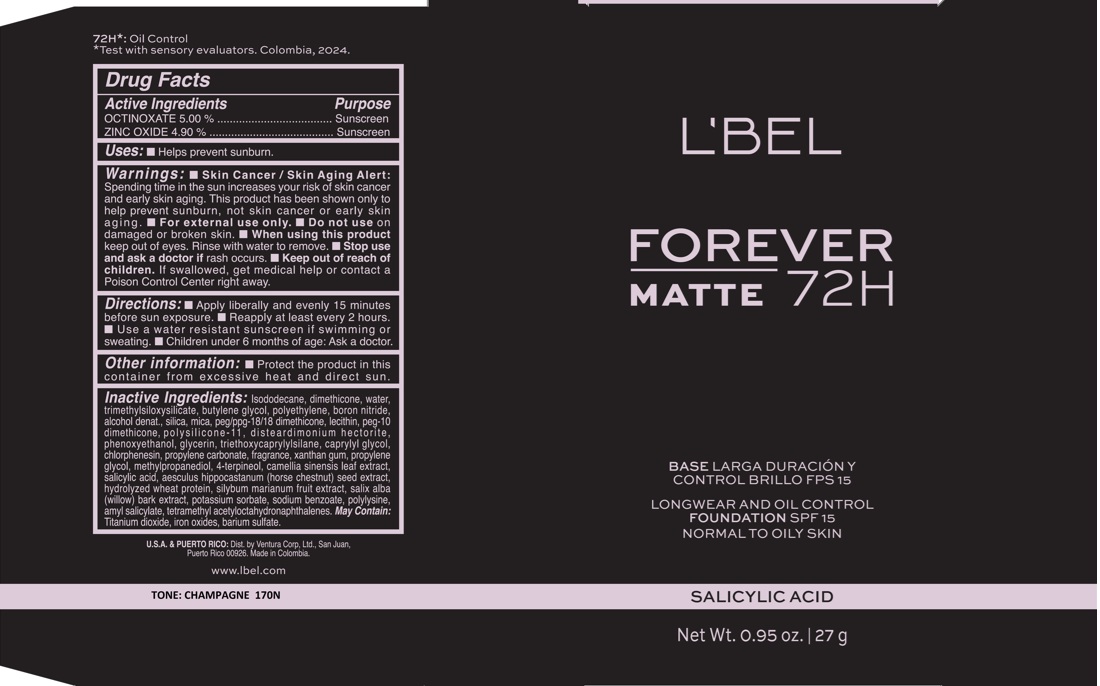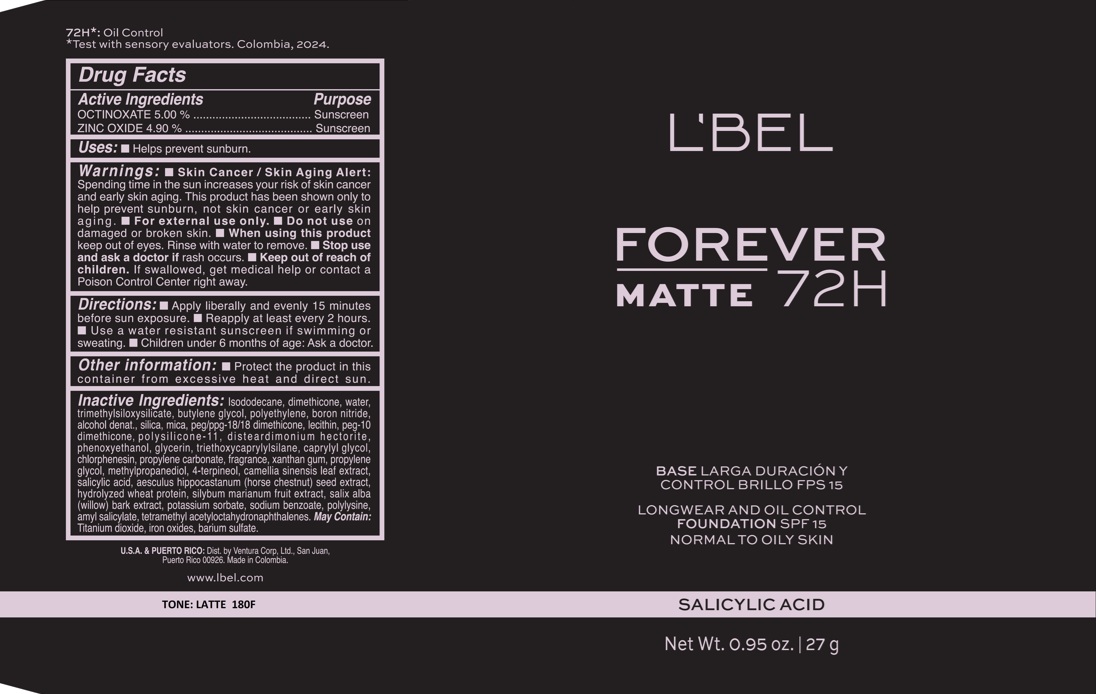 DRUG LABEL: LBEL FOREVER MATTE LONGWEAR AND CONTROL FOUNDATION 72H SPF 15 ALMENDRA 230N
NDC: 14141-403 | Form: EMULSION
Manufacturer: BEL STAR S.A.
Category: otc | Type: HUMAN OTC DRUG LABEL
Date: 20250424

ACTIVE INGREDIENTS: ZINC OXIDE 49 mg/1 g; OCTINOXATE 50 mg/1 g
INACTIVE INGREDIENTS: METHYLPROPANEDIOL; SODIUM BENZOATE; AMYL SALICYLATE; BARIUM SULFATE; PHENOXYETHANOL; POLYETHYLENE; ALCOHOL; HYDROLYZED WHEAT PROTEIN (ENZYMATIC, 3000 MW); MICA; TRIETHOXYCAPRYLYLSILANE; HORSE CHESTNUT; ISODODECANE; SALICYLIC ACID; MILK THISTLE; POTASSIUM SORBATE; TETRAMETHYL ACETYLOCTAHYDRONAPHTHALENES; SILICON DIOXIDE; PEG/PPG-18/18 DIMETHICONE; GLYCERIN; CAPRYLYL GLYCOL; XANTHAN GUM; CHLORPHENESIN; POLY-L-LYSINE (30000-70000 MW); CI 77491; CI 77492; 4-TERPINEOL; TRIMETHYLSILOXYSILICATE (M/Q 0.6-0.8); BORON NITRIDE; PROPYLENE GLYCOL; GREEN TEA LEAF; SALIX ALBA BARK; TITANIUM DIOXIDE; CI 77499; LECITHIN, SUNFLOWER; PEG-10 DIMETHICONE (200 CST); DISTEARDIMONIUM HECTORITE; DIMETHICONE; WATER; BUTYLENE GLYCOL; PROPYLENE CARBONATE

LBEL FOREVER MATTE LONGWEAR AND OIL CONTROL FOUNDATION 72H SPF 15

Active Ingredients

OCTINOXATE 5.00%

ZINC OXIDE 4.90%

Purpose

Sunscreen

Uses

- Helps prevent sunburn

Warnings

- Skin Cancer / Skin Aging Alert: Spending time in the sun increases your risk of skin cancer and early skin aging. This product has been shown only to help prevent sunburn, not skin cancer or early skin aging.
- For external use only.

Do not use

on damaged or broken skin.

When using this product

keep out of eyes. Rinse with water to remove.

Stop use and ask a doctor if

rash occurs.

Keep out of reach of children.

If swallowed, get medical help or contact a Poison Control Center right away.

Directions

- Apply liberally and evenly 15 minutes before sun exposure.
- Reapply at least every 2 hours
- Use a water resistant sunscreen if swimming or sweating.
- Children under 6 months of age: Ask a doctor

Other information

- Protect the product in this container from excessive heat and direct sun.

Inactive ingredients

Isododecane, dimethicone, water, trimethylsiloxysilicate, butylene glycol, polyethylene, boron nitride, alcohol denat., silica, mica, peg/ppg-18/18 dimethicone, lecithin, peg-10 dimethicone, polysilicone-11, disteardimonium hectorite, phenoxyethanol, glycerin, triethoxycaprylylsilane, caprylyl glycol, chlorphenesin, propylene carbonate, fragrance, xanthan gum, propylene glycol, methylpropanediol, 4-terpineol, camellia sinensis leaf extract, salicylic acid, aesculus hippocastanum (horse chestnut) seed extract, hydrolyzed wheat protein, silybum marianum fruit extract, ‎salix alba ‎(‎willow‎) ‎bark ‎extract, potassium sorbate, sodium benzoate, polylysine, amyl salicylate, tetramethyl acetyloctahydronaphthalenes.

May Contain:

Titanium dioxide, iron oxides, barium sulfate.